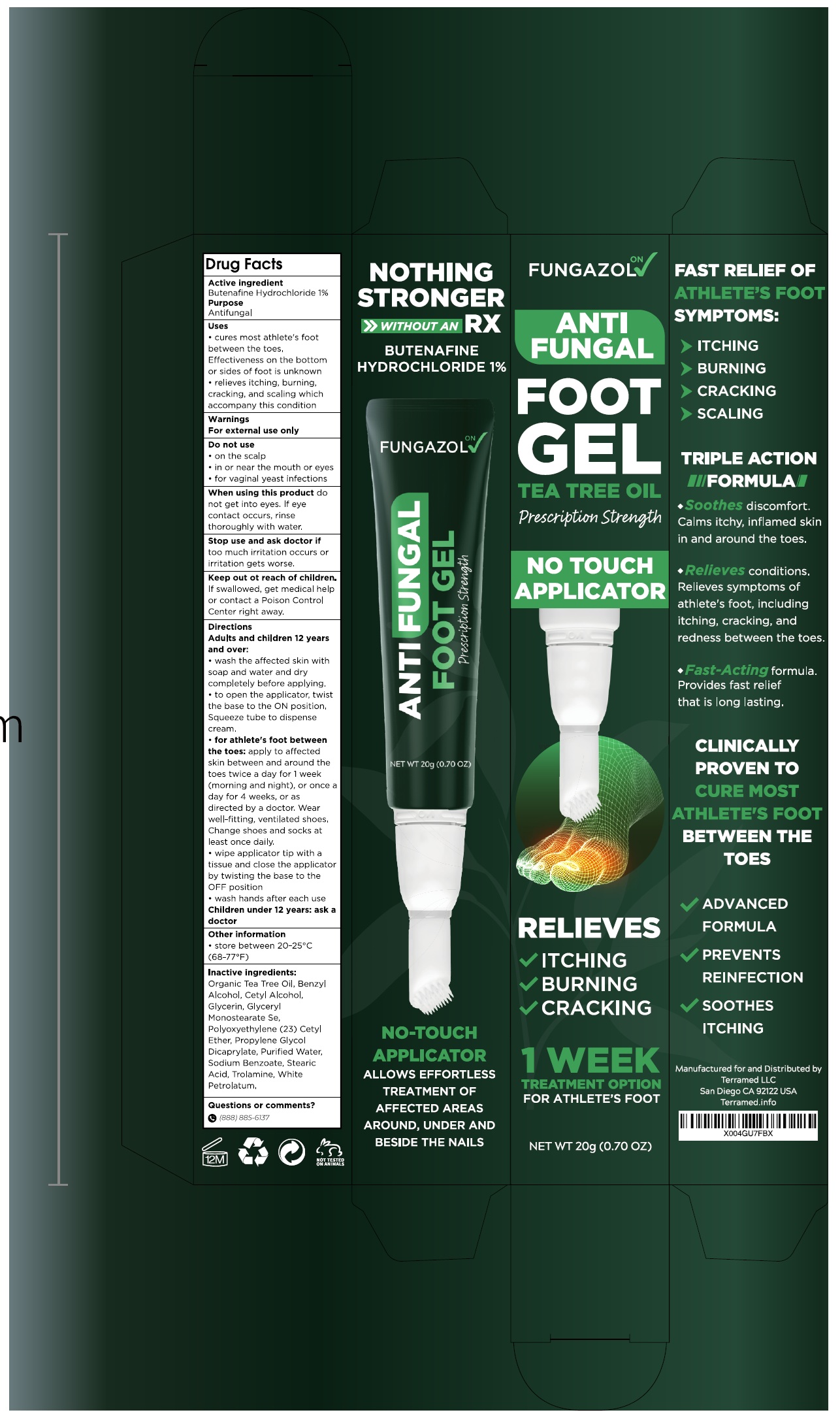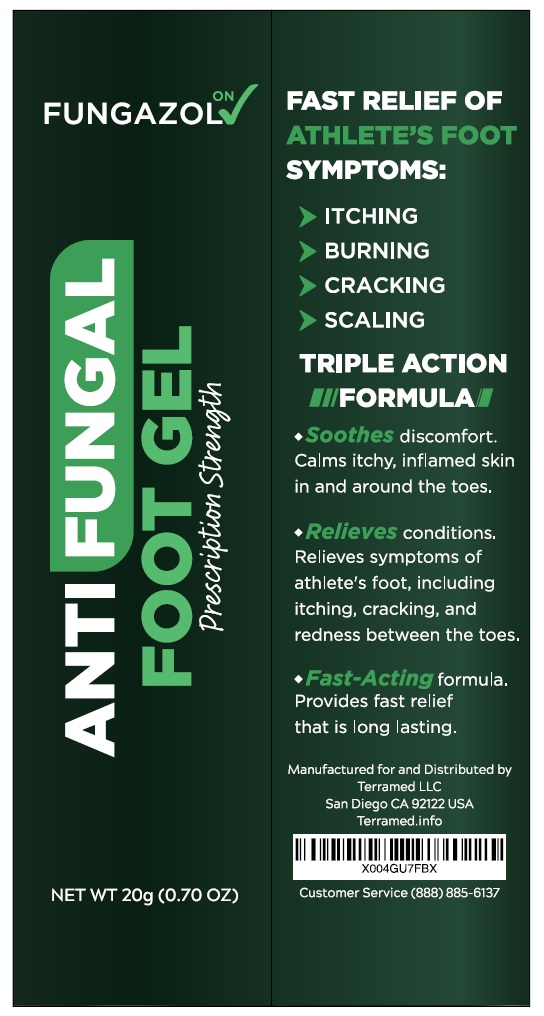 DRUG LABEL: Antifungal Foot Treatment
NDC: 83004-016 | Form: GEL
Manufacturer: Rida LLC
Category: homeopathic | Type: HUMAN OTC DRUG LABEL
Date: 20250306

ACTIVE INGREDIENTS: BUTENAFINE HYDROCHLORIDE 10 mg/1 g
INACTIVE INGREDIENTS: TEA TREE OIL; BENZYL ALCOHOL; CETYL ALCOHOL; GLYCERIN; GLYCERYL STEARATE SE; CETETH-23; PROPYLENE GLYCOL DICAPRYLATE; WATER; SODIUM BENZOATE; STEARIC ACID; TROLAMINE; PETROLATUM

Active Ingredient

Butenafine hydrochloride 1%

Purpose

Antifungal

Uses

● cures most athlete's foot between the toes. Effectiveness on the bottom or sides of foot is unknown.
● relieves itching, burning, cracking, and scaling which accompany these conditions

Warnings

For external use only

Do not use

- on nails or scalp
- in or near the mouth or the eyes
- or vaginal yeast infections

- When using this productdo not get into the eyes. If eye contact occurs, rinse thoroughly with water.
- Stop use and ask a doctor iftoo much irritation occurs or irritation gets worse
- Keep out of reach of children.If swallowed, get medical help or contact a Poison Control Center right away.

Directions

● adults and children 12 years and over:
● wash the affected skin with the soap and water and dry completly before applying.
● to open the applicator, twist the base to the ON position. Squeeze tube to dispence cream.

● for athlete's foot between the toes: apply to affected skin between and around the toes twice a day for 1 week (morning and night), or once a day for 4 weeks, or as directed by a doctor. Wear well-fitting, ventilated shoes. Change shoes and socks at least once daily.

- Wipe applicator tip with a tissue and close the applicator by twisting the base to the OFF position
- wash hands after each use.

Childern under 12 years: ask a doctor

Other Information

● store between 20º to 25º C (68º to 77º F)

Inactive ingredients

Tea Tree Oil, benzyl alcohol, cetyl alcohol, glycerin, glyceryl monostearate SE, polyoxyethylene (23) cetyl ether, propylene glycol dicaprylate, purified water, sodium benzoate, stearic acid, trolamine, white petrolatum